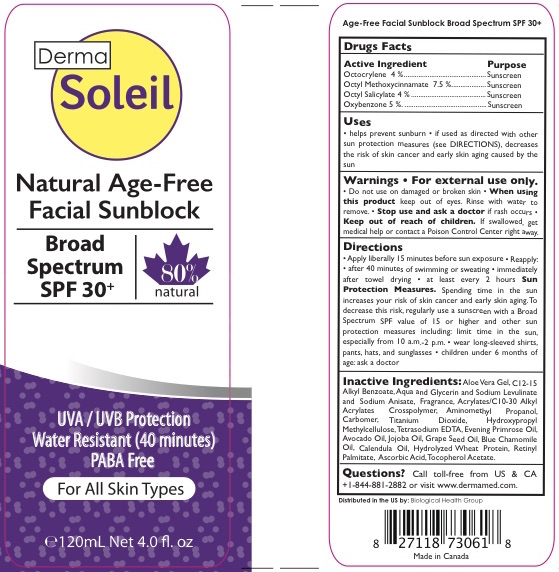 DRUG LABEL: DERMA SOLEIL NATURAL AGE-FREE FACIAL SUNBLOCK SPF 30
NDC: 69711-905 | Form: LOTION
Manufacturer: Deserving Health International Corp.
Category: otc | Type: HUMAN OTC DRUG LABEL
Date: 20200221

ACTIVE INGREDIENTS: OXYBENZONE 5 g/100 mL; OCTOCRYLENE 4 g/100 mL; OCTINOXATE 7.5 g/100 mL; OCTISALATE 4 g/100 mL
INACTIVE INGREDIENTS: EDETATE SODIUM; JOJOBA OIL; GRAPE SEED OIL; EVENING PRIMROSE OIL; ASCORBIC ACID; SODIUM ANISATE; AMINOMETHYLPROPANOL; CARBOXYPOLYMETHYLENE; GLYCERIN; CALENDULA OFFICINALIS FLOWER; HYDROLYZED WHEAT PROTEIN (ENZYMATIC; 3000 MW); VITAMIN A PALMITATE; ALKYL (C12-15) BENZOATE; SODIUM LEVULINATE; AVOCADO OIL; CHAMOMILE FLOWER OIL; GLYCERYL CAPRYLATE; CARBOMER COPOLYMER TYPE A (ALLYL PENTAERYTHRITOL CROSSLINKED); HYPROMELLOSES; ALOE VERA LEAF; .ALPHA.-TOCOPHEROL ACETATE; WATER; CARBOMER INTERPOLYMER TYPE A (55000 CPS); TITANIUM DIOXIDE

DERMA SOLEIL NATURAL AGE-FREE FACIAL SUNBLOCK SPF 30

ACTIVE INGREDIENT

Octocrylene 4%
Octyl Methoxycinnamate 7.5%,
Octyl Salicylate 4%,
Oxybenzone 5%

PURPOSE

Sunscreen

WHEN USING

Helps prevent sunburn
If used as directed with other sun protection measures (see DIRECTIONS), decreases the risk of skin cancer and early skin aging caused by the sun.

WARNINGS

For external use only.

Do not use on damaged or broken skin. Stop use and ask a doctor if rash occurs.

When using this product keep out of eyes. Rinse with water to remove.

Keep out of reach of children. If swallowed, get medical help or contact a poison control center right away.

INACTIVE INGREDIENT

Aloe Vera Gel, C12-15 Alkyl Benzoate, Aqua and Glycerin and Sodium Levulinate and Sodium Anisate, Fragrance, Acrylates/C10-30 Alkyl Acrylates Crosspolymer, Aminomethyl Propanol, Carbomer, Titanium Dioxide, Hydroxypropyl Methylcellulose, Tetrasodium EDTA, Evening Primrose Oil, Avocado Oil, Jojoba Oil, Grape Seed Oil, Blue Chamomile Oil, Calendula Oil, Hydrolyzed Wheat Protein, Retinyl Palmitate, Ascorbic Acid, Tocopherol Acetate.